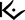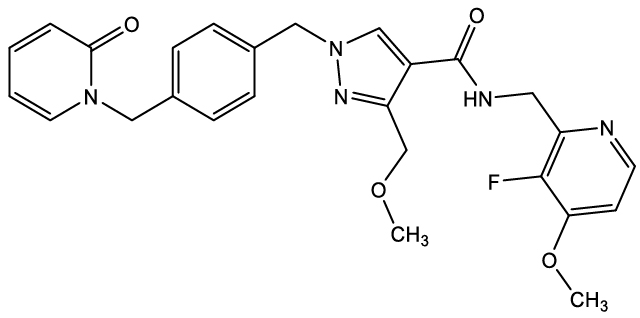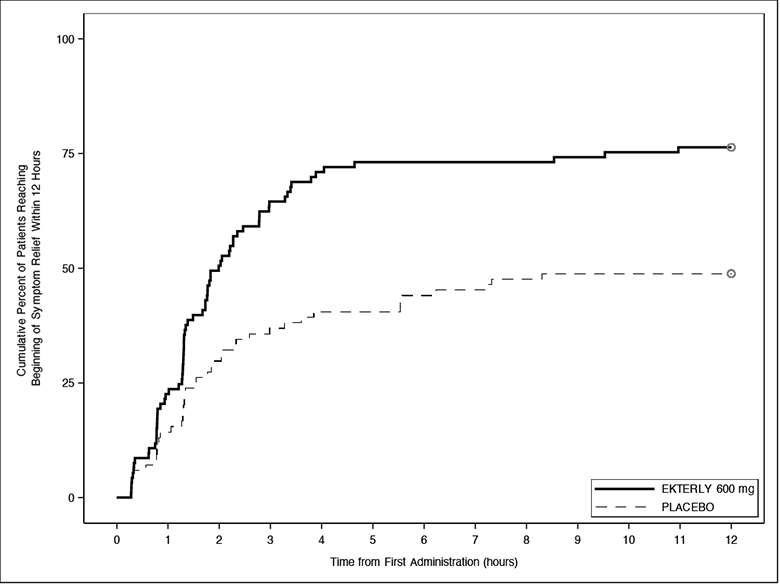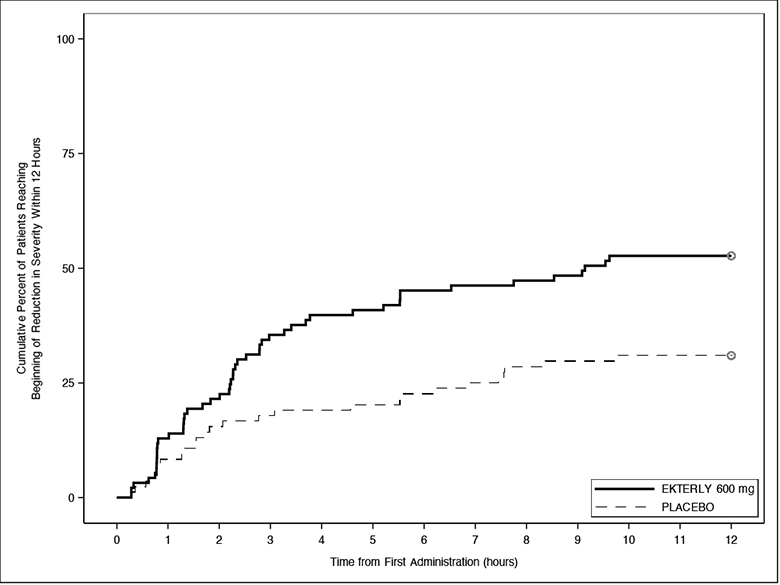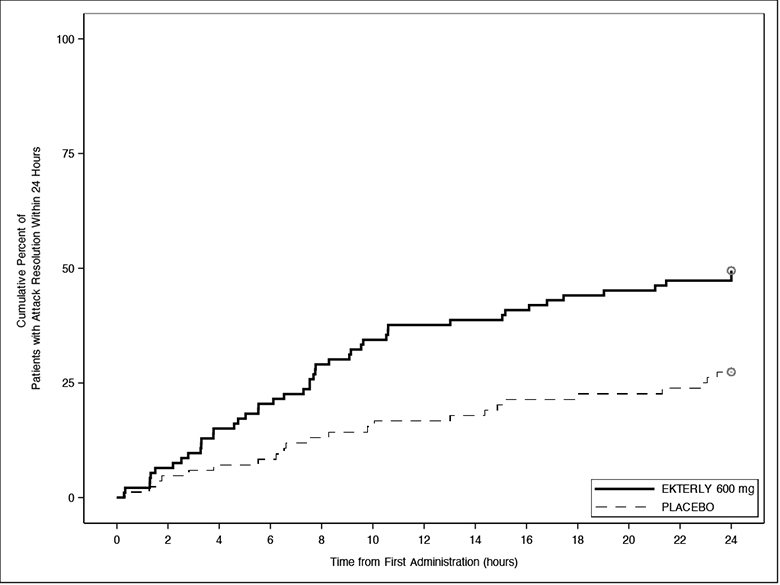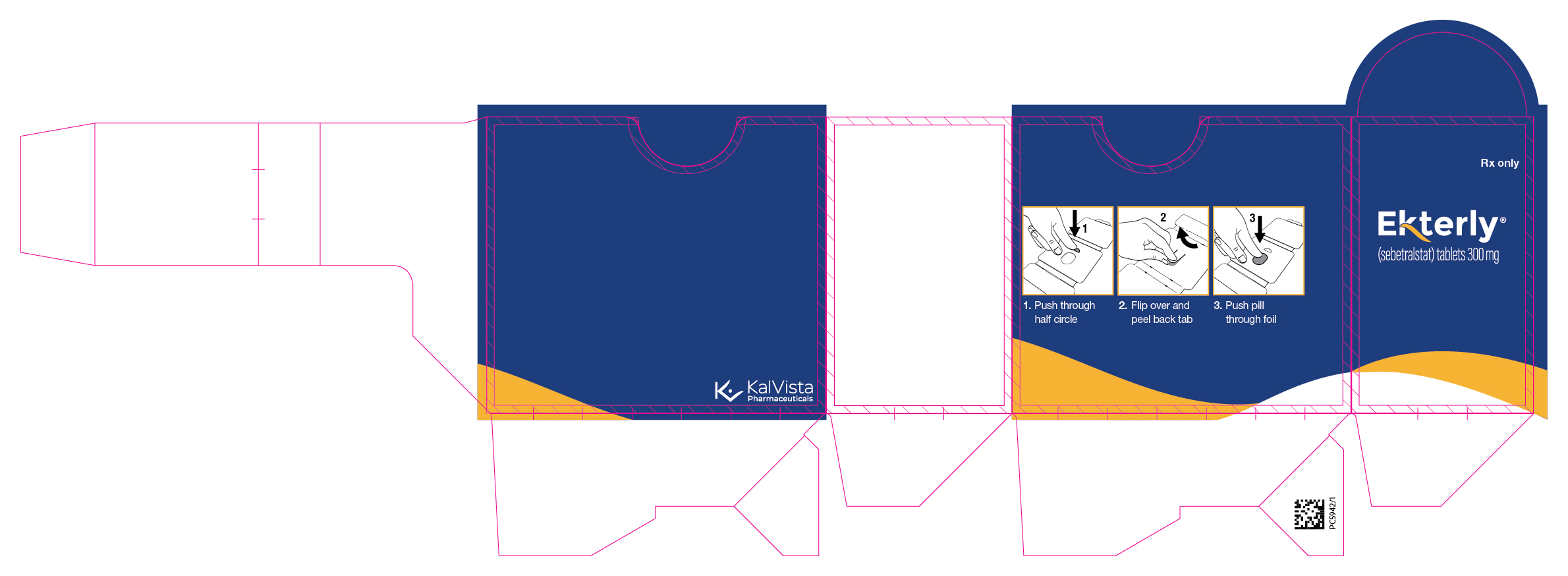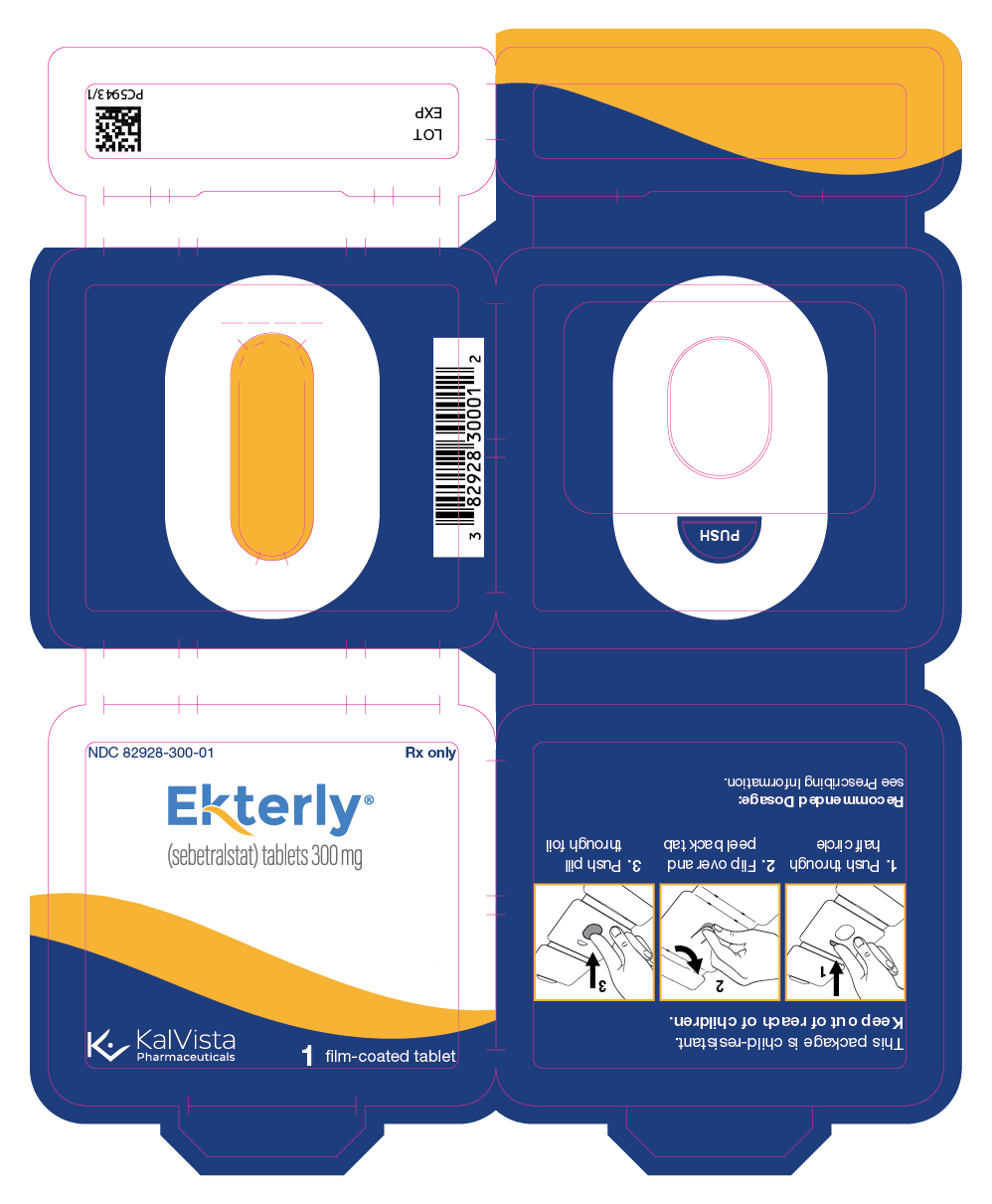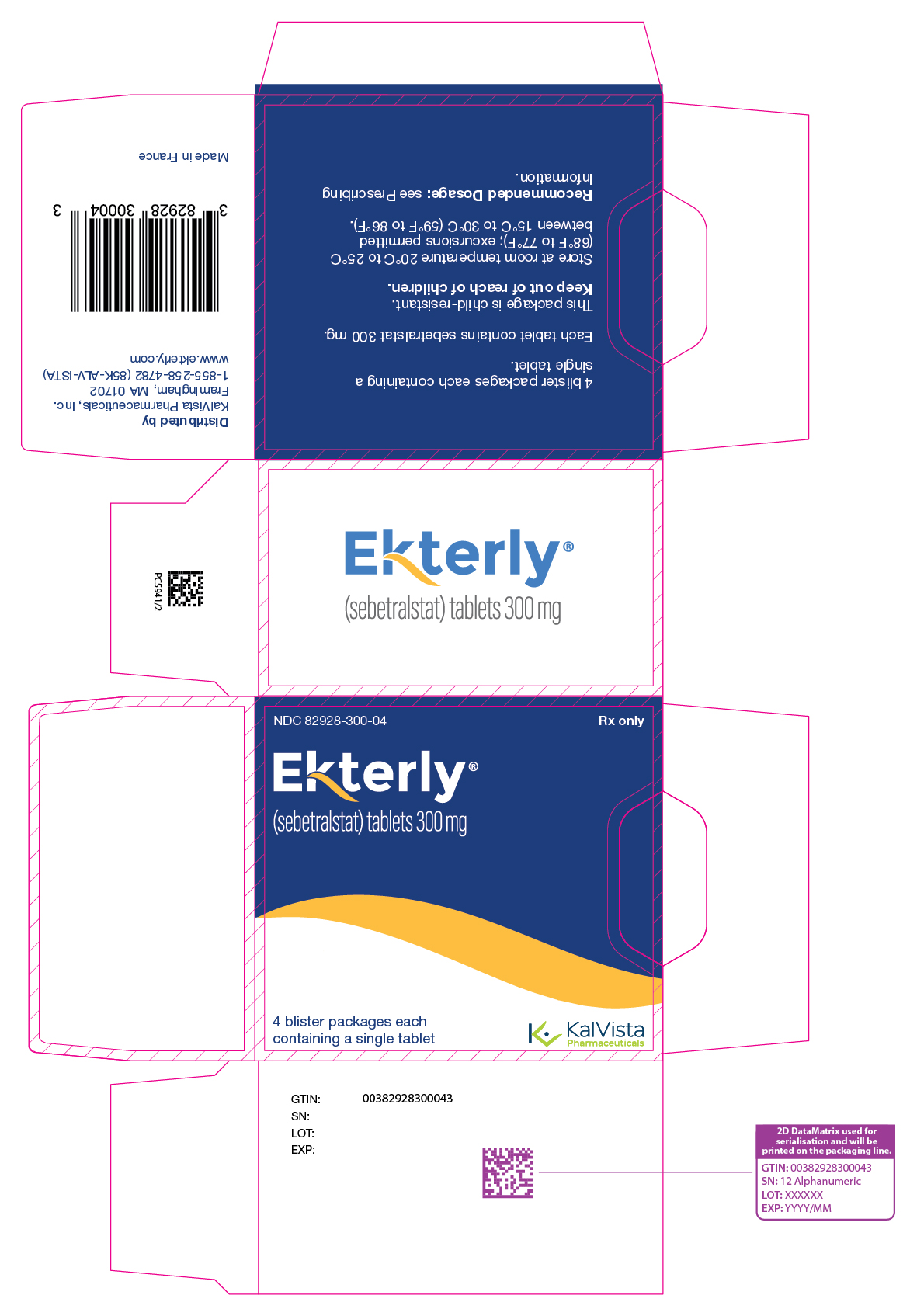 DRUG LABEL: EKTERLY
NDC: 82928-300 | Form: TABLET
Manufacturer: KalVista Pharmaceuticals Ltd
Category: prescription | Type: HUMAN PRESCRIPTION DRUG LABEL
Date: 20251119

ACTIVE INGREDIENTS: Sebetralstat 300 mg/1 1
INACTIVE INGREDIENTS: MICROCRYSTALLINE CELLULOSE 101; CROSCARMELLOSE SODIUM; POVIDONE K30; MAGNESIUM STEARATE; POLYVINYL ALCOHOL GRAFT POLYETHYLENE GLYCOL COPOLYMER (3:1; 45000 MW); TALC; TITANIUM DIOXIDE; GLYCERYL MONO- AND DICAPRYLOCAPRATE; POLYVINYL ALCOHOL, UNSPECIFIED; FERROSOFERRIC OXIDE; MALTODEXTRIN; GUAR GUM; HYPROMELLOSE, UNSPECIFIED; MEDIUM-CHAIN TRIGLYCERIDES; FERRIC OXIDE YELLOW

HIGHLIGHTS OF PRESCRIBING INFORMATION

These highlights do not include all the information needed to use EKTERLY safely and effectively. See full prescribing information for EKTERLY.
EKTERLY (sebetralstat) tablets, for oral use
Initial U.S. Approval: 2025

1 INDICATIONS AND USAGE

EKTERLY® is a plasma kallikrein inhibitor indicated for the treatment of acute attacks of hereditary angioedema (HAE) in adult and pediatric patients aged 12 years and older. (1)

2 DOSAGE AND ADMINISTRATION

Recommended Dosage: one dose of 600 mg (2 tablets) taken orally at the earliest recognition of an HAE attack. (2.1)

- A second dose of 600 mg (2 tablets) may be taken 3 hours after the first dose if response is inadequate, or if symptoms worsen or recur. (2.1)
- Maximum Recommended Dosage: 1,200 mg in any 24-hour period. (2.1)
- See full prescribing information for dosage modification for concomitant use with CYP3A4 inhibitors and inducers. (2.2)
- See full prescribing information for recommended dosage for patients with hepatic impairment. (2.3)

3 DOSAGE FORMS AND STRENGTHS

Tablets: 300 mg (3)

4 CONTRAINDICATIONS

None (4)

6 ADVERSE REACTIONS

The most common adverse reaction (incidence ≥2%) is headache. (6.1)

To report SUSPECTED ADVERSE REACTIONS, contact KalVista Pharmaceuticals, Inc. at 1-855-258-4782 or FDA at 1-800-FDA-1088 or www.fda.gov/medwatch.

7 DRUG INTERACTIONS

- Strong and Moderate CYP3A4 Inhibitors: Avoid use with strong CYP3A4 inhibitors. In patients taking moderate CYP3A4 inhibitors, take one dose of 300 mg. A second dose of 300 mg may be taken at least 3 hours after the first dose if response is inadequate, or if symptoms worsen or recur. (2.2, 7.1, 12.3)
- CYP3A4 Inducers: Avoid use with moderate or strong CYP3A4 inducers. (2.2, 7.1, 12.3)

8 USE IN SPECIFIC POPULATIONS

Hepatic Impairment: Avoid use of EKTERLY in patients with severe hepatic impairment (Child-Pugh Class C). In patients with moderate hepatic impairment (Child-Pugh Class B) take one dose of 300 mg. A second dose of 300 mg may be taken at least 3 hours after the first dose if response is inadequate, or if symptoms worsen or recur. (2.3, 8.6, 12.3)

FULL PRESCRIBING INFORMATION

1 INDICATIONS AND USAGE

EKTERLY® is indicated for the treatment of acute attacks of hereditary angioedema (HAE) in adult and pediatric patients aged 12 years and older.

2 DOSAGE AND ADMINISTRATION

2.1 Recommended Dosage

The recommended dosage of EKTERLY is one dose of 600 mg (two tablets) orally at the earliest recognition of an acute HAE attack.

- A second dose of 600 mg (two tablets) may be taken at least 3 hours after the first dose if response is inadequate, or if symptoms worsen or recur.
- Maximum recommended dosage is 1,200 mg (four tablets) in any 24-hour period.

2.2 Dosage Modification for CYP3A4 Inhibitors and Inducers

Refer to Table 1 for dosage modification of EKTERLY when used concomitantly with CYP3A4 inhibitors and inducers.

Table 1: Dosage Modification of EKTERLY for Concomitant use with CYP3A4 Inhibitors and Inducers
Dosage Modification for Concomitant use of EKTERLY with CYP3A4 Inhibitors
Strong CYP3A4 Inhibitors | Avoid concomitant use with EKTERLY.
Moderate CYP3A4 Inhibitors | Reduce EKTERLY dosage to 300 mg (one tablet) orally at earliest recognition of an acute HAE attack.; A second dose of 300 mg (one tablet) may be taken at least 3 hours after first dose if response is inadequate or if symptoms worsen or recur [see Drug Interactions (7.1) and Clinical Pharmacology (12.3)].
Weak CYP3A4 Inhibitors | No dosage modification of EKTERLY [see Dosage and Administration (2.1)].
Dosage Modification for Concomitant use of EKTERLY with CYP3A4 Inducers
Strong and Moderate CYP3A4 Inducers | Avoid concomitant use with EKTERLY.
Weak CYP3A4 Inducers | No dosage modification of EKTERLY [see Dosage and Administration (2.1)].

2.3 Recommended Dosage in Patients with Hepatic Impairment

Refer to Table 2 for recommended dosage of EKTERLY in patients with hepatic impairment.

Table 2: Recommended Dosage of EKTERLY in Patients with Hepatic Impairment
Recommended Dosage of EKTERLY in Patients with Hepatic Impairment
Severe Hepatic Impairment (Child-Pugh Class C) | Avoid use of EKTERLY [see Use in Specific Populations (8.6) and Clinical Pharmacology (12.3)].
Moderate Hepatic Impairment (Child-Pugh Class B) | Recommended dosage of EKTERLY is one dose of 300 mg (one tablet) orally at the earliest recognition of an acute HAE attack. A second dose of 300 mg (one tablet) may be taken at least 3 hours after the first dose if response is inadequate, or if symptoms worsen or recur [see Use in Specific Populations (8.6) and Clinical Pharmacology (12.3)].
Mild Hepatic Impairment (Child-Pugh Class A) | Recommended dosage is the same as the recommended dosage in patients with normal hepatic function [see Dosage and Administration (2.1)].

3 DOSAGE FORMS AND STRENGTHS

Tablets: 300 mg, yellow, oval, biconvex, film-coated tablets debossed with on one side and “300” on the other side.

4 CONTRAINDICATIONS

None.

6 ADVERSE REACTIONS

6.1 Clinical Trials Experience

Because clinical trials are conducted under widely varying conditions, adverse reaction rates observed in the clinical trials of a drug cannot be directly compared to rates in the clinical trials of another drug and may not reflect the rates observed in practice.

The safety of EKTERLY is based on data from a double-blind, randomized, placebo-controlled, three-way, crossover clinical trial (KONFIDENT) [see Clinical Studies (14)]. In KONFIDENT, a total of 110 patients aged 12 years and older with HAE treated 264 attacks. In the safety population, 93 patients received EKTERLY 600 mg, 86 patients received EKTERLY 300 mg, and 83 patients received placebo. While EKTERLY 300 mg was included in KONFIDENT, the safety data is based on the recommended dosage of EKTERLY 600 mg.

Table 3 displays adverse reaction(s) with an incidence of ≥2% in the EKTERLY 600 mg treated patients and more common than placebo.

Table 3: Adverse Reaction(s) with EKTERLY with Incidence ≥2% and More Common than Placebo in Patients with Hereditary Angioedema (KONFIDENT)
Adverse Reaction | EKTERLY 600 mg (N = 93) | Placebo (N = 83)a
Adverse Reaction | n (%) | n (%)
Headache | 3 (3.2) | 1 (1.2)
aOne (1) patient assigned to administer placebo actually received EKTERLY 600 mg. Safety results are presented by actual treatment received.

7 DRUG INTERACTIONS

7.1 Effect of Other Drugs on EKTERLY

Strong CYP3A4 Inhibitors

- Avoid use of EKTERLY with strong CYP3A4 inhibitors [see Clinical Pharmacology (12.3)].

Sebetralstat is a substrate of CYP3A4. Concomitant use of sebetralstat with a strong CYP3A4 inhibitor increases sebetralstat exposure, which may increase the risk of sebetralstat adverse reactions.

Moderate and Weak CYP3A4 Inhibitors

- Reduce dose of EKTERLY to one dose of 300 mg (one tablet) orally at the earliest recognition of an HAE attack when used concomitantly with moderate CYP3A4 inhibitors. A second dose of 300 mg (one tablet) may be taken at least 3 hours after the first dose if response is inadequate, or if symptoms worsen or recur [see Dosage and Administration (2.2) and Clinical Pharmacology (12.3)].

Sebetralstat is a substrate of CYP3A4. Concomitant use of sebetralstat with a moderate CYP3A4 inhibitor increases sebetralstat exposure, which may increase the risk of sebetralstat adverse reactions.

- No dose modification is recommended when EKTERLY is used concomitantly with a weak CYP3A4 inhibitor [see Dosage and Administration (2.1) and Clinical Pharmacology (12.3)].

Strong and Moderate CYP3A4 Inducers

- Use of EKTERLY with strong or moderate CYP3A4 inducers is not recommended.

Sebetralstat is a substrate of CYP3A4. Concomitant use of sebetralstat with a strong or moderate CYP3A4 inducer decreases sebetralstat exposure, which may decrease efficacy.

Weak CYP3A4 Inducers

No dose modification is recommended when EKTERLY is used concomitantly with weak CYP3A4 inducers [see Clinical Pharmacology (12.3)].

8 USE IN SPECIFIC POPULATIONS

8.1 Pregnancy

Risk Summary

There are no available data on EKTERLY in pregnant women to evaluate for a drug-associated risk of major birth defects, miscarriage or other adverse maternal or fetal outcomes. In animal reproduction studies, oral administration of sebetralstat to pregnant rats and rabbits during organogenesis produced no evidence of fetal harm with dose exposures up to approximately 15 and 11 times, respectively, the human exposure at the maximum recommended human dose (MRHD) of up to 1,200 mg (on an area under the curve [AUC] basis). Sebetralstat produced an increase in embryofetal losses and fetal malformations in rats at an exposure that was 60 times the MRHD (see Data).

The estimated background risk of major birth defects and miscarriage for the indicated population is unknown. All pregnancies have a background risk of birth defect, loss, or other adverse outcomes. In the U.S. general population, the estimated background risk of major birth defects and miscarriages in clinically recognized pregnancies is 2% to 4% and 15% to 20%, respectively.

Data

Animal Data

In an embryofetal development study with pregnant rats dosed by the oral route during the period of organogenesis from gestation days 6 to 17, sebetralstat caused a dose-related increase in the incidence of external and visceral malformations, described as cleft palates and ventricular septal defects and an increase in embryofetal losses (early and late fetal deaths, mean number of live fetuses, and post-implantation loss at an exposure that was 60 times the MRHD (on an AUC basis with a maternal dose of 600 mg/kg/day)). Maternal toxicity, as evidenced by decreased body weight gains, was observed at exposures 60 times the MRHD (on an AUC basis with a maternal oral dose of 600 mg/kg/day). No fetal or maternal toxicities were observed at exposures up to 15 times the MRHD (on an AUC basis with a maternal oral dose of 300 mg/kg/day).

In an embryofetal development study with pregnant rabbits dosed by the oral route during the period of organogenesis from gestation days 6 to 18, maternal toxicity was evidenced by a decrease in body weight gain at an exposure that was 11 times the MRHD (on an AUC basis with a maternal dose of 300 mg/kg/day). No adverse effects on maternal toxicity were observed at an exposure that was 2 times the MRHD (on an AUC basis with a maternal dose of 100 mg/kg/day). No adverse effects on fetal toxicity were observed at an exposure that was 11 times the MRHD (on an AUC basis with a maternal oral dose of 300 mg/kg/day).

In a prenatal and postnatal development study with pregnant rats dosed by the oral route during the periods of gestation and lactation from gestation day 6 to lactation day 20, sebetralstat had no effects on the growth and development of offspring at an exposure that was 40 times the MRHD (on an AUC basis with a maternal oral dose of 450 mg/kg/day).

8.2 Lactation

Risk Summary

There are no data on the presence of sebetralstat or its metabolites in human milk, the effects on the breastfed infant, or the effects on milk production. Radioactivity is present in animal milk after dosing with radiolabeled sebetralstat. When a drug is present in animal milk, it is likely that the drug will be present in human milk. Data in the rat have shown excretion of sebetralstat and/or its metabolites in milk (see Data). The developmental and health benefits of breastfeeding should be considered along with the mother’s clinical need for EKTERLY and any potential adverse effects on the breastfed child from EKTERLY or from the underlying maternal condition.

Data

Animal Data

In a single dose placental transfer and milk secretion study in lactating rats dosed with radiolabeled sebetralstat by the oral route, total radioactivity was detected in fetal plasma at 1 hour post dose. Similar concentrations of total radioactivity were observed in the milk and plasma of lactating females, with the maximum radioactive concentration observed at 1 hour post dose that returned to background levels by 24 hours post dose. The concentration of total radioactivity in animal milk does not necessarily predict the concentration of drug in human milk.

8.4 Pediatric Use

The safety and effectiveness of EKTERLY for treatment of acute attacks of hereditary angioedema (HAE) have been established in pediatric patients aged 12 years and older. Use of EKTERLY for this indication is supported by evidence from an adequate and well-controlled study (KONFIDENT) in adults and pediatric patients aged 12 years and older with additional population pharmacokinetic (PK) analysis from adults and pediatric patients aged 12 years and older, which showed no clinically significant differences in PK based on body weight or age. Results of the subgroup analysis for pediatric patients aged 12 years and older were consistent with study results for adult patients [see Adverse Reactions (6.1), Clinical Pharmacology (12.3), and Clinical Studies (14)].

The safety and effectiveness of EKTERLY in pediatric patients aged <12 years of age have not been established.

8.5 Geriatric Use

Clinical studies of EKTERLY did not include sufficient numbers of patients 65 years of age and older to determine whether they respond differently from younger adult patients.

8.6 Hepatic Impairment

No dose adjustment of EKTERLY is recommended for patients with mild hepatic impairment (Child-Pugh Class A). For patients with moderate hepatic impairment (Child-Pugh Class B), the recommended dose of EKTERLY is one dose of 300 mg (one tablet) orally at the earliest recognition of an HAE attack. A second dose of 300 mg (one tablet) may be taken at least 3 hours after the first dose if response is inadequate, or if symptoms worsen or recur. Avoid use of EKTERLY in patients with severe hepatic impairment (Child-Pugh Class C) [see Dosage and Administration (2.3) and Clinical Pharmacology (12.3)].

10 OVERDOSAGE

Consider contacting the poison control help line (1-800-222-1222) or medical toxicologist for overdose management recommendations.

11 DESCRIPTION

The active ingredient of EKTERLY is sebetralstat, a plasma kallikrein inhibitor. The chemical name of sebetralstat is N-[(3-fluoro-4-methoxypyridin-2-yl) methyl]-3-(methoxymethyl)-1-({4-[(2-oxo-1,2-dihydropyridin-1-yl) methyl]phenyl}methyl)-1H-pyrazole-4-carboxamide. The chemical structure of sebetralstat is:

The molecular formula is C26H26FN5O4 and molecular weight is 491.5. Sebetralstat is a white to off-white crystalline powder. It is slightly soluble in ethanol, acetone and isopropanol, and practically insoluble in water.

EKTERLY is supplied as 300 mg film-coated tablets for oral administration. Each tablet contains the active ingredient sebetralstat. The inactive ingredients include croscarmellose sodium, glycerol mono and dicaprylocaprate, guar gum/guar galactomannan, hypromellose, iron oxide black, iron oxide yellow, macrogol polyvinyl alcohol graft copolymer, magnesium stearate, maltodextrin, medium chain triglycerides, microcrystalline cellulose, polyvinyl alcohol, povidone, talc and titanium dioxide.

12 CLINICAL PHARMACOLOGY

12.1 Mechanism of Action

Sebetralstat is a competitive, reversible inhibitor of plasma kallikrein. Plasma kallikrein is a serine protease that cleaves high molecular weight kininogen (HK) releasing bradykinin which increases vascular permeability through activation of bradykinin receptors causing edema. Sebetralstat inhibits the cleavage of HK and reduces production of bradykinin, thereby treating the clinical symptoms of an acute, episodic attack of HAE. Sebetralstat also inhibits the positive feedback mechanism of the kallikrein kinin system by plasma kallikrein, thereby reducing factor XIIa and additional plasma kallikrein generation.

12.2 Pharmacodynamics

Concentration-dependent inhibition of plasma kallikrein, measured as a reduction from baseline of specific enzyme activity, was observed in exploratory assays. Following administration of a single oral dose of 600 mg sebetralstat to healthy subjects, greater than 90% mean inhibition of plasma kallikrein activity was observed beginning at 30 minutes after dosing and maintained through about 6 hours post-dose.

Cardiac Electrophysiology

The largest mean increase in QTc interval was 10.4 msec (upper confidence interval = 15.3 msec) after administration of sebetralstat (2.5 times the maximum recommended dose) in healthy subjects. The increase in the QTc interval was concentration dependent.

12.3 Pharmacokinetics

Following a single oral dose of 600 mg sebetralstat in subjects with HAE, the geometric mean (CV%) Cmax is 6,080 ng/mL (40%) and AUC0-inf is 17,600 ng•h/mL (36%). Following administration of a second oral dose of 600 mg sebetralstat 3 hours after the first dose, Cmax increases 10% and AUC0-inf increases 90% when compared to those observed following a single dose.

No clinically relevant differences in sebetralstat pharmacokinetics were observed between healthy subjects and patients with HAE.

Absorption

After a single oral dose of 600 mg sebetralstat, the median time to peak plasma concentration is approximately 1 hour.

Effect of Food

No clinically relevant differences in sebetralstat pharmacokinetics were observed following administration of a high-fat meal (900-1,000 calories in total – 500-600, 250 and 150 calories from fat, carbohydrate and protein respectively).

Distribution

The estimated typical apparent volume of distribution (Vz/F) for sebetralstat is 70.1 L (95% CI: 64.8, 75.4). Sebetralstat plasma protein binding is 77% in vitro.

Elimination

Following administration of a single oral dose of 600 mg sebetralstat, the mean (SD) elimination half-life of sebetralstat ranged from 5.3 (2.3) to 8.9 (5.1) hours. The estimated typical apparent clearance (CL/F) is 30.7 L/h (95% CI: 29.1, 32.2).

Metabolism

Sebetralstat is primarily metabolized by CYP3A4 and to a lesser extent by CYP2C8.

Excretion

Following administration of a single oral dose of 600 mg radiolabeled sebetralstat to healthy male subjects, approximately 63% of the dose was recovered in feces (12.5% as unchanged sebetralstat) and 32% in urine (8.7% as unchanged sebetralstat).

Specific Populations

No clinically relevant differences in the pharmacokinetics of sebetralstat were observed based on body weight (45-135 kg), age (19-68 years), sex, race (71% White, 17% Black, 11% Asian), and mild renal impairment (eGFR 60-89 mL/min/1.73 m^2). The effect of moderate and severe renal impairment (eGFR <60 mL/min/1.73 m^2) on sebetralstat pharmacokinetics is unknown.

Patients with Hepatic Impairment

The pharmacokinetics of sebetralstat were evaluated in subjects with mild (Child-Pugh Class A) and moderate (Child-Pugh Class B) hepatic impairment following administration of a single 600 mg dose. In subjects with mild hepatic impairment Cmax was increased by 7% and AUC increased by 16% compared to subjects with normal hepatic function. In subjects with moderate hepatic impairment Cmax was increased by 63% and AUC was increased by 100% compared to subjects with normal hepatic function. The effect of severe hepatic impairment (Child-Pugh Class C) on sebetralstat pharmacokinetics is unknown [see Use in Specific Populations (8.6)].

Drug Interaction Studies

Clinical Studies and Model-Informed Approaches

Strong CYP3A4 Inhibitors: Sebetralstat Cmax increased 2.4-fold and AUC0-inf increased 5.2-fold following concomitant administration with itraconazole (a strong CYP3A4 inhibitor) 200 mg once daily for 6 days [see Drug Interactions (7.1)].

Moderate CYP3A4 Inhibitors: Sebetralstat Cmax increased 1.8-fold and AUC0-inf increased 2-fold following concomitant administration with verapamil (a moderate CYP3A4 inhibitor) 240 mg once daily for 6 days [see Drug Interactions (7.1)].

Strong CYP3A4 Inducers: Sebetralstat Cmax decreased by 66% and AUC0-inf decreased by 83% following concomitant administration with phenytoin (a strong CYP3A4 inducer) 100 mg three times daily for 15 days [see Drug Interactions (7.1)].

Moderate CYP3A4 Inducers: Sebetralstat Cmax decreased by 63% and AUC0-inf decreased by 79% following concomitant administration with efavirenz (a moderate CYP3A4 inducer) 600 mg once daily for 14 days [see Drug Interactions (7.1)].

Acid-Reducing Agents: Sebetralstat Cmax is estimated to decrease by up to 56% and AUC0-inf is estimated to decrease by up to 30% at pH 6 relative to pH 0.5.

Other Drugs: No clinically significant differences in sebetralstat pharmacokinetics were observed when administered concomitantly with quinidine (P-gp inhibitor), eltrombopag (BCRP inhibitor), cimetidine (evaluated as a weak CYP3A4 inhibitor), or modafinil (weak CYP3A4 inducer).

In Vitro Studies

CYP450 Enzymes: Sebetralstat is a substrate of CYP3A4 and CYP2C8, and is not a substrate of CYP1A2, CYP2A6, CYP2B6, CYP2C9, CYP2C19, CYP2D6, or CYP2E1. Sebetralstat is an inhibitor of CYP2C9 and CYP3A4. Sebetralstat did not inhibit CYP1A2, CYP2B6, CYP2C8, CYP2C19, or CYP2D6.

Transporter Systems: Sebetralstat is a substrate of P-gp and BCRP, and is not a substrate of OATP1B1, OATP1B3, OAT1, OAT3, OCT2, or MATE1. Sebetralstat is an inhibitor of BCRP, OATP1B1, OATP1B3, OAT3, OCT2, MATE1, MATE2-K, and BSEP. Sebetralstat did not inhibit P-gp or OAT1.

13 NONCLINICAL TOXICOLOGY

13.1 Carcinogenesis, Mutagenesis, Impairment of Fertility

Carcinogenesis

A 6-month carcinogenicity study in rasH2-Tg transgenic mice was conducted to assess the carcinogenic potential of sebetralstat. Sebetralstat demonstrated no tumorigenic potential in a study with male and female mice that received oral doses up to 200 mg/kg/day and 300 mg/kg/day, respectively.

Mutagenesis

Sebetralstat was not mutagenic or clastogenic in the following assays: in vitro bacterial reverse mutation (Ames) test, in vitro chromosomal aberration assay in human peripheral blood lymphocytes, and in vivo rat micronucleus assay.

Impairment of Fertility

Fertility and reproductive performance were unaffected in male or female rats that received sebetralstat by the oral route at dose levels up to 600 mg/kg/day (approximately 38 times the MRHD in adults on an AUC basis).

14 CLINICAL STUDIES

The efficacy of EKTERLY for the treatment of acute attacks of hereditary angioedema (HAE) in adult and pediatric patients aged 12 years and older was evaluated in a double-blind, randomized, placebo-controlled, multicenter crossover clinical trial (KONFIDENT [NCT05259917]). KONFIDENT employed a 3-way, complete crossover design comparing EKTERLY 600 mg and EKTERLY 300 mg to placebo. If needed (as determined by the patient) a second dose could be administered after 3 hours. Patients were required to treat an eligible HAE attack prior to crossover to the next treatment period. Severe laryngeal attacks were not treated in KONFIDENT. The duration of trial participation was approximately 25 weeks. Although evaluated in KONFIDENT, EKTERLY 300 mg is not a recommended dose for treatment of acute HAE attacks.

The demographics and baseline characteristics of patients in KONFIDENT are provided in Table 4.

Table 4: Demographics and Baseline Characteristics of Patients in KONFIDENT Trial
 | KONFIDENT (N=110)
Female, n (%) | 66 (60)
Mean age, years (SD) | 38 (15)
12 to <18 years, n (%) | 13 (12)
≥18 years, n (%) | 97 (88)
Race, n (%)
Asian | 10 (9)
Black or African American | 1 (1)
White | 92 (84)
Other | 1 (1)
Not reported | 6 (5)
Hispanic or Latino, n (%) | 7 (6)
HAE Type I, n (%) | 101 (92)
Background HAE prophylaxis, n (%) | 24 (22)

A total of 110 patients were randomized and experienced at least one HAE attack. Of the 264 treated HAE attacks, 142 (54%) had peripheral symptoms only, 85 (32%) had abdominal symptoms only, 27 (10%) had abdominal and peripheral symptoms, 8 (3%) had mild to moderate laryngeal symptoms, and 2 (1%) had missing attack location.

The primary endpoint for KONFIDENT was the ‘time to beginning of symptom relief’ defined as at least “a little better” at two consecutive time points within 12 hours of first dose administration, assessed using a seven-point scale Patient Reported Global Impression of Change (PGI-C) ranging from “much worse” to “much better”.

As shown in Figure 1, there was a statistically significant faster time to the beginning of symptom relief for EKTERLY 600 mg compared to placebo. A total of 71 out of 93 (76%) patients administered EKTERLY 600 mg and 41 out of 84 (49%) patients administered placebo achieved the primary endpoint. The median time to beginning of symptom relief within 12 hours of first dose was 2.0 hours (95% CI: 1.5, 2.8) in patients administered EKTERLY 600 mg.

Figure 1: Kaplan-Meier for Time to Beginning of Symptom Relief Within 12 Hours of First Dose Administration with EKTERLY in KONFIDENT

Note: In the EKTERLY 600 mg group, 38% of patients administered a second dose within 12 hours.

Less than 50% of placebo patients reached beginning of symptom relief within 12 hours; therefore, the median time could not be estimated.

Patients who did not achieve the endpoint, received alternate on-demand therapy, or lacked at least 2 consecutive post-baseline assessments were right-censored at 12 hours.

Secondary Endpoints

The first key secondary endpoint was the ‘time to first incidence of reduction in severity’ at two consecutive time points within 12 hours of first dose administration, assessed using a five-point scale Patient Global Impression of Severity (PGI-S) ranging from “none” to “severe”.

The ‘time to first incidence of reduction in severity’ (Figure 2) was statistically significantly faster for EKTERLY 600 mg compared to placebo. A total of 49 out of 93 (53%) patients administered EKTERLY 600 mg and 26 out of 84 (31%) patients administered placebo achieved reduction in severity within 12 hours. The median time to achieve this endpoint was 9.1 hours (95% CI: 3.8, not reached) in patients administered EKTERLY 600 mg.

Figure 2: Kaplan-Meier for Time to First Incidence of Reduction in Severity Within 12 Hours of First Dose Administration with EKTERLY in KONFIDENT

Note: In the EKTERLY 600 mg group, 38% of patients administered a second dose within 12 hours.

Less than 50% of placebo patients reached beginning of reduction in severity within 12 hours; therefore, the median time could not be estimated.

Patients who did not achieve the endpoint, received alternate on-demand therapy, or lacked at least 2 consecutive post-baseline assessments were right-censored at 12 hours.

The second key secondary endpoint was ‘time to attack resolution’ defined as PGI-S of “none” within 24 hours of first dose administration.

The ‘time to attack resolution’ (Figure 3) was statistically significantly faster for EKTERLY 600 mg compared to placebo. A total of 46 out of 93 (49%) patients administered EKTERLY 600 mg and 23 out of 84 (27%) patients administered placebo achieved attack resolution within 24 hours.

Figure 3: Kaplan-Meier for Time to Attack Resolution Within 24 Hours of First Dose Administration with EKTERLY in KONFIDENT

Note: In the EKTERLY 600 mg group, 39% of patients administered a second dose within 24 hours.

Less than 50% of EKTERLY 600 mg and placebo patients had attack resolution within 24 hours; therefore, the median time could not be estimated.

Patients who did not achieve the endpoint, received alternate on-demand therapy, or lacked post-baseline assessments were right-censored at 24 hours.

Other Endpoints

The time to beginning of at least “better” at two consecutive time points on the PGI-C within 12 hours of the first dose administration was assessed. A total of 54 out of 93 (58%) patients administered EKTERLY 600 mg and 21 out of 84 (25%) patients administered placebo achieved this endpoint. The median time was 4.6 hours (95% CI: 3.3, 9.5) in patients administered EKTERLY 600 mg.

16 HOW SUPPLIED/STORAGE AND HANDLING

EKTERLY (sebetralstat) tablets: 300 mg, yellow, oval, biconvex, film-coated tablets debossed with on one side and “300” on the other side.

- EKTERLY is supplied in a carton containing four child-resistant blister cards. Each child-resistant blister card contains 1 x 300 mg tablet (NDC 82928-300-04).
- Each carton contains a tamper evident seal. Do not use if tamper evident seal is broken or missing.

Store at 20°C to 25°C (68°F to 77°F). Excursions permitted between 15°C and 30°C (59°F to 86°F) [see USP Controlled Room Temperature].

17 PATIENT COUNSELING INFORMATION

Advise patients to read the FDA-approved patient labeling (Patient Information).

Dosage Modification for Strong and Moderate CYP3A4 Inhibitors

Advise patients not to use EKTERLY with strong CYP3A4 inhibitors [see Drug Interactions (7.1) and Clinical Pharmacology (12.3)]. When used concomitantly with moderate CYP3A4 inhibitors, advise patients to reduce dose to one tablet of 300 mg (total dose 300 mg) at the earliest recognition of an HAE attack. A second dose of 300 mg (one tablet) may be taken at least 3 hours after the first dose if response is inadequate, or if symptoms worsen or recur [see Dosage and Administration (2.2), Drug Interactions (7.1) and Clinical Pharmacology (12.3)].

Recommended Dosage in Patients with Hepatic Impairment

Advise patients with severe hepatic impairment to avoid use of EKTERLY. In patients with moderate hepatic impairment, advise patients to take one tablet of 300 mg (total dose 300 mg) at earliest recognition of an HAE attack. A second dose of 300 mg (one tablet) may be taken at least 3 hours after the first dose if response is inadequate, or if symptoms worsen or recur [see Use in Specific Populations (8.6) and Clinical Pharmacology (12.3)].

For more information, visit www.EKTERLY.com

EKTERLY® is a registered trademark of KalVista Pharmaceuticals Limited.

Distributed by:
KalVista Pharmaceuticals, Inc.
200 Crossing Boulevard
Framingham, MA 01702

PATIENT INFORMATION
EKTERLY (ek-TURR-lee)
(sebetralstat)
tablets, for oral use

What is EKTERLY?

- EKTERLY is a prescription medicine used to treat sudden (acute) attacks of hereditary angioedema (HAE) in adults and children aged 12 years of age and older.
- It is not known if EKTERLY is safe and effective in children under 12 years of age.

Before you take EKTERLY, tell your healthcare provider about all of your medical conditions, including if you:

- are pregnant or planning to become pregnant. It is not known if EKTERLY can harm your unborn baby.
- are breastfeeding or plan to breastfeed. It is not known if EKTERLY passes into your breastmilk. Talk to your healthcare provider about the best way to feed your baby while taking EKTERLY.
- have liver problems.

Tell your healthcare provider about all of the medicines you take, including prescription and over-the-counter medicines, vitamins, and herbal supplements.

- Taking EKTERLY with certain other medicines can cause side effects or affect how well EKTERLY or the other medicines work.

Especially tell your healthcare provider if you take any of the following, as their use with EKTERLY is not recommended:

- itraconazole
- phenytoin
- efavirenz

Know the medicines you take. Keep a list of them to show your healthcare provider or pharmacist when you get a new medicine.

How should I take EKTERLY?

- Take EKTERLY exactly as your healthcare provider tells you to take it.
- Take 2 tablets, by mouth, at the earliest sign of an acute attack of hereditary angioedema. If you do not feel better or if your symptoms worsen or come back, take another dose (2 tablets) at least 3 hours after the first dose.
- Your healthcare provider may change how much EKTERLY you receive if you take certain medicines or if you have liver problems:
  - Take 1 tablet, by mouth, at the earliest sign of an acute attack of hereditary angioedema. If you do not feel better or if your symptoms worsen or come back take another dose (1 tablet) at least 3 hours after the first dose.
- If you take too much EKTERLY, call your healthcare provider or Poison Help line at 1-800-222-1222 or go to the nearest hospital emergency room right away.

What are the possible side effects of EKTERLY?
The most common side effects of EKTERLY include:

- headache

For more information, ask your healthcare provider or pharmacist.
Call your doctor for medical advice about side effects. You may report side effects to FDA at 1-800-FDA-1088.

How should I store EKTERLY?

- Store EKTERLY in the blister package that it comes in.
- Store EKTERLY at room temperature between 68°F to 77°F (20°C to 25°C).

Keep EKTERLY and all medicines out of the reach of children.

General information about the safe and effective use of EKTERLY
Medicines are sometimes prescribed for purposes other than those listed in a Patient Information leaflet. Do not use EKTERLY for a condition for which it was not prescribed. Do not give EKTERLY to other people, even if they have the same symptoms that you have. It may harm them. You can ask your pharmacist or healthcare provider for information about EKTERLY that is written for health professionals.

What are the ingredients in EKTERLY?

Active ingredient: sebetralstat

Inactive ingredients: croscarmellose sodium, glycerol mono and dicaprylocaprate, guar gum/guar galactomannan, hypromellose, iron oxide black, iron oxide yellow, macrogol polyvinyl alcohol graft copolymer, magnesium stearate, maltodextrin, medium chain triglycerides, microcrystalline cellulose, polyvinyl alcohol, povidone, talc and titanium dioxide.

Distributed by KalVista Pharmaceuticals, Inc, 200 Crossing Boulevard, Framingham, MA 01702
EKTERLY is a registered trademark of KalVista Pharmaceuticals Limited
©2025 KalVista Pharmaceuticals, Inc. All rights reserved.
For more information, visit www.EKTERLY.com or call 1-855-258-4782.

This Patient Information has been approved by the U.S. Food and Drug Administration Issued: 07/2025

PACKAGE LABEL

Telescopic Pack (outer)

Telescopic Pack (inner)

Wallet Card